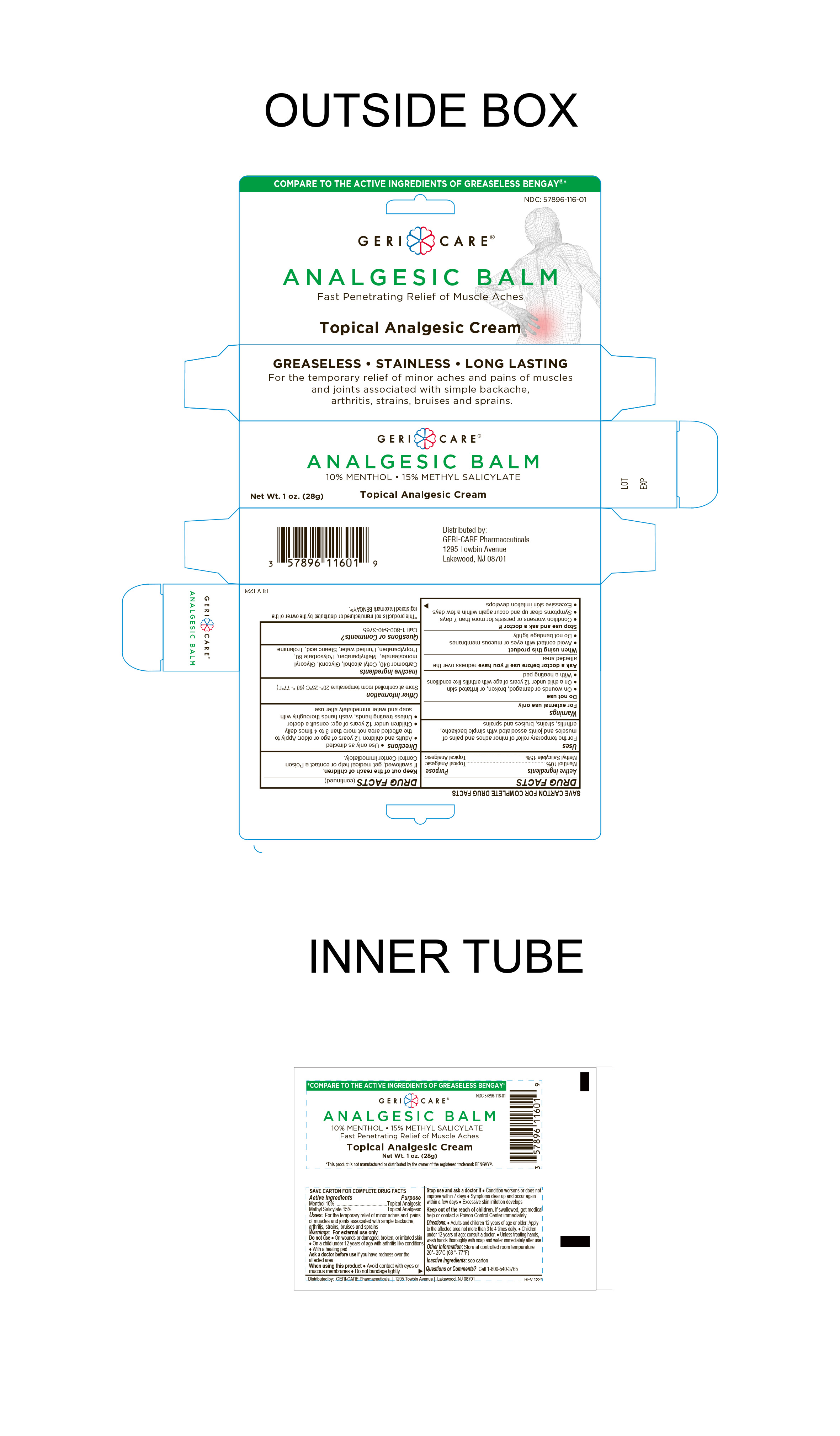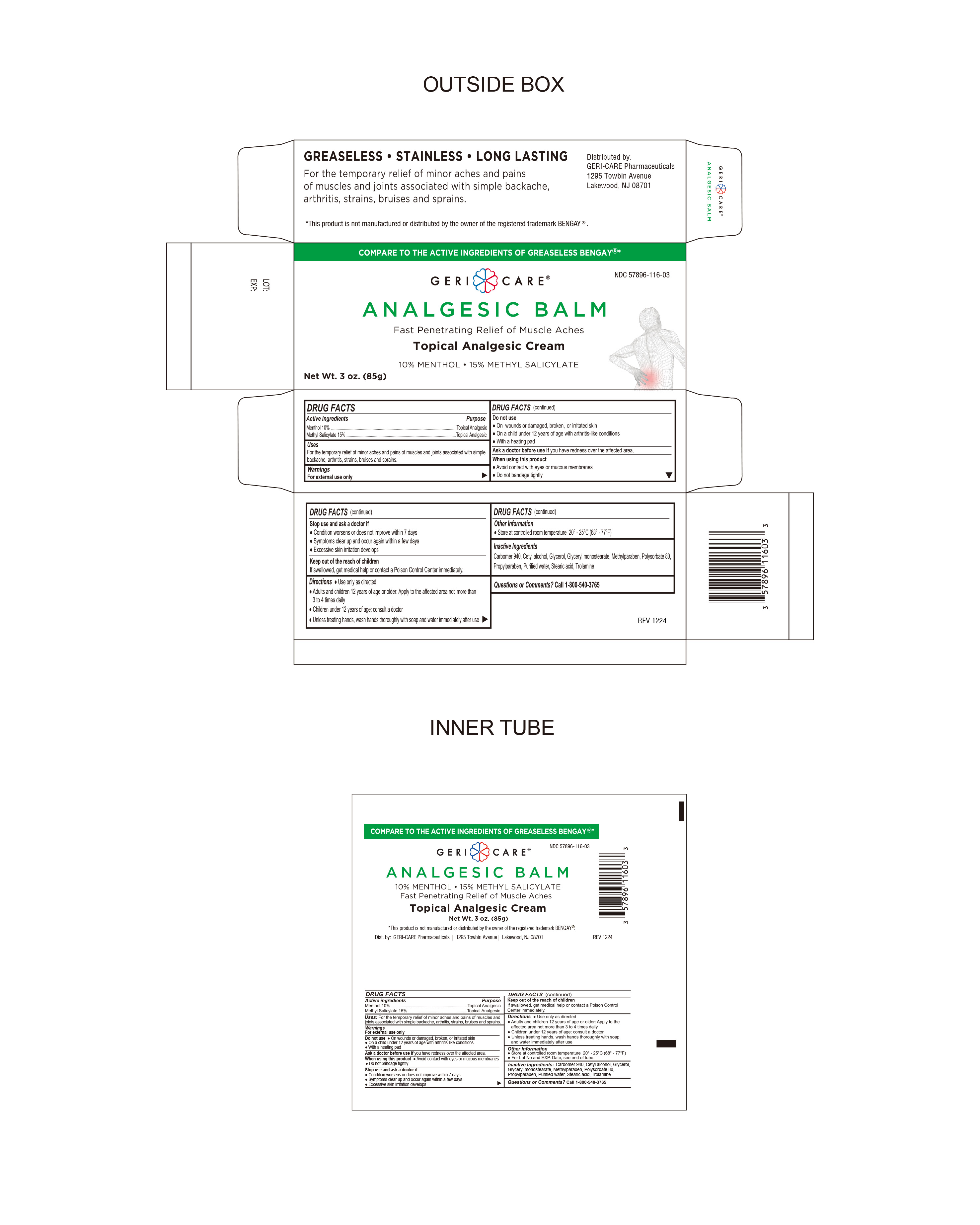 DRUG LABEL: Analgesic Balm
NDC: 57896-116 | Form: CREAM
Manufacturer: Geri-Care Pharmaceuticals, Corp
Category: otc | Type: HUMAN OTC DRUG LABEL
Date: 20251118

ACTIVE INGREDIENTS: MENTHOL 10 g/100 g; METHYL SALICYLATE 15 g/100 g
INACTIVE INGREDIENTS: POLYSORBATE 80; TROLAMINE; CARBOMER 940; CETYL ALCOHOL; GLYCERYL MONOSTEARATE; METHYLPARABEN; WATER; STEARIC ACID; GLYCERIN; PROPYLPARABEN

GERI-CARE Analgesic Balm

Active Ingredient

Menthol 10%

Active Ingredient

Methyl Salicylate 15%

PURPOSE

Topical Analgesic

INDICATIONS AND USAGE

For the temporary relief of minor aches and pains of muscles and joints associated with simple backache, arthritis, strains, bruises and sprains

Warnings

For external use only

Do not use:

- On wounds or damaged, broken (open) or irritated skin
- On a child under 12 years of age with arthritis-like conditions
- With a heating pad

Ask a doctor before use if you have redness over the affected area.

When using this product

- Avoid contact with eyes or mucous membranes
- Do not bandage tightly

Stop Use and ask a doctor

- Conditions worsens or does not improve within 7 days
- Symptoms clear up and occur again within a few days
- Excessive skin irritation develops

Keep out of the reach of Children

If swallowed, get medical help or contact a Poison Control Center immediately

Directions

- Use only as directed
- Adults and children 12 years of age or older. Apply to the affected area not more than 3 to 4 times daily.

Children under 12 years of age. consult a doctor

- Unless treating hands, wash hands thoroughly with soap and water immediately after use.

Other Information

- Store at controlled room temperature 20º-25ºC (68º-77ºF)

Questions ? Call 1-800-540-3765

Inactive Ingredients

Carbomer 940, Cetyl alcohol, Glycerol, Glyceryl monostearate, Methylparaben, Polysorbate 80, Propylparaben, Purified Water, Stearic acid, Trolamine

Distributed By

GeriCare Pharmaceuticals

1650 63rd Street

Brooklyn, NY 11204

Made in China